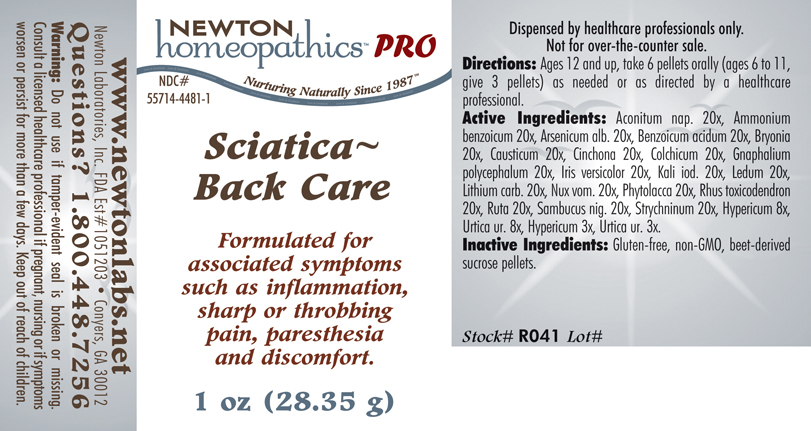 DRUG LABEL: Sciatica - Back Care 
NDC: 55714-4481 | Form: PELLET
Manufacturer: Newton Laboratories, Inc.
Category: homeopathic | Type: HUMAN PRESCRIPTION DRUG LABEL
Date: 20110601

ACTIVE INGREDIENTS: Aconitum Napellus 20 [hp_X]/1 g; Ammonium Benzoate 20 [hp_X]/1 g; Arsenic Trioxide 20 [hp_X]/1 g; Benzoic Acid 20 [hp_X]/1 g; Bryonia Alba Root 20 [hp_X]/1 g; Causticum 20 [hp_X]/1 g; Cinchona Officinalis Bark 20 [hp_X]/1 g; Pseudognaphalium Obtusifolium 20 [hp_X]/1 g; Iris Versicolor Root 20 [hp_X]/1 g; Potassium Iodide 20 [hp_X]/1 g; Ledum Palustre Twig 20 [hp_X]/1 g; Lithium Carbonate 20 [hp_X]/1 g; Strychnos Nux-vomica Seed 20 [hp_X]/1 g; Phytolacca Americana Root 20 [hp_X]/1 g; Toxicodendron Pubescens Leaf 20 [hp_X]/1 g; Ruta Graveolens Flowering Top 20 [hp_X]/1 g; Sambucus Nigra Flowering Top 20 [hp_X]/1 g; Strychnine 20 [hp_X]/1 g; Hypericum Perforatum 8 [hp_X]/1 g; Urtica Urens 8 [hp_X]/1 g; Colchicum Autumnale Bulb 20 [hp_X]/1 g
INACTIVE INGREDIENTS: Sucrose

Sciatica - Back Care

INDICATIONS & USAGE SECTION

Sciatica - Back Care Formulated for associated symptoms such as inflammation, sharp or throbbing pain, paresthesia and discomfort.

DOSAGE & ADMINISTRATION SECTION

Directions: Ages 12 and up, take 6 pellets orally (ages 6 to 11, give 3 pellets) as needed or as directed by a healthcare professional.

ACTIVE INGREDIENT SECTION

Aconitum nap. 20x, Ammonium benzoicum 20x, Arsenicum alb. 20x, Benzoicum acidum 20x, Bryonia 20x, Causticum 20x, Cinchona 20x, Colchicum 20x, Gnaphalium polycephalum 20x, Iris versicolor 20x, Kali iod. 20x, Ledum 20x, Lithium carb. 20x, Nux vom. 20x, Phytolacca 20x, Rhus toxicodendron 20x, Ruta 20x, Sambucus nig. 20x, Strychninum 20x, Hypericum 8x, Urtica ur. 8x, Hypericum 3x, Urtica ur. 3x.

PURPOSE SECTION

Formulated for associated symptoms such as inflammation, sharp or throbbing pain, paresthesia and discomfort.

INACTIVE INGREDIENT SECTION

Inactive Ingredients: Gluten-free, non-GMO, beet-derived sucrose pellets.

QUESTIONS? SECTION

www.newtonlabs.net Newton Laboratories, Inc. FDA Est # 1051203 - Conyers, GA 30012
Questions? 1.800.448.7256

WARNINGS SECTION

Warning: Do not use if tamper - evident seal is broken or missing. Consult a licensed healthcare professional if pregnant, nursing or if symptoms worsen or persist for more than a few days. Keep out of reach of children.

PREGNANCY OR BREAST FEEDING SECTION

Consult a licensed healthcare professional if pregnant, nursing or if symptoms worsen or persist for more than a few days

KEEP OUT OF REACH OF CHILDREN SECTION

Keep out of reach of children